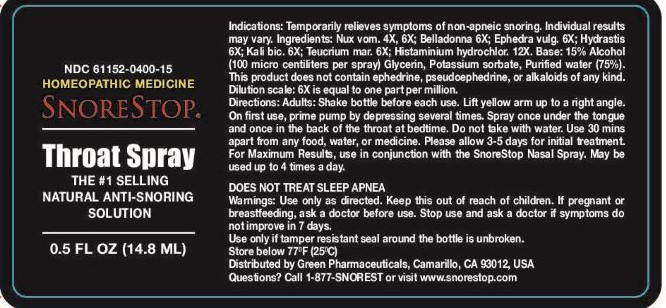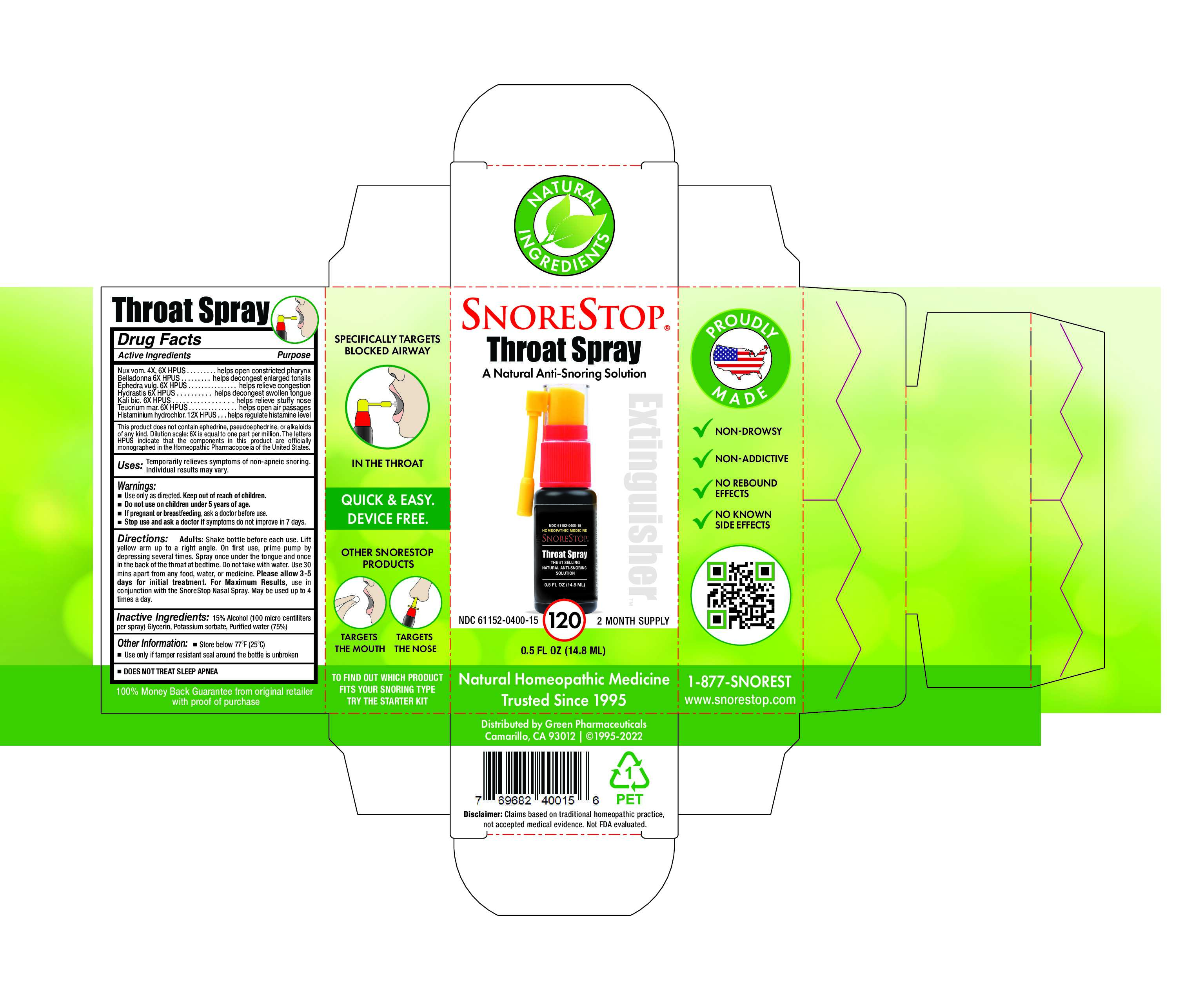 DRUG LABEL: SnoreStop Extinguisher 120
NDC: 61152-400 | Form: SPRAY
Manufacturer: Green Pharmaceuticals Inc
Category: homeopathic | Type: HUMAN OTC DRUG LABEL
Date: 20250108

ACTIVE INGREDIENTS: ATROPA BELLADONNA 6 [hp_X]/4.5 mL; EPHEDRA DISTACHYA FLOWERING TWIG 6 [hp_X]/4.5 mL; HISTAMINE DIHYDROCHLORIDE 12 [hp_X]/4.5 mL; GOLDENSEAL 6 [hp_X]/4.5 mL; POTASSIUM DICHROMATE 6 [hp_X]/4.5 mL; STRYCHNOS NUX-VOMICA SEED 6 [hp_X]/4.5 mL; TEUCRIUM MARUM 6 [hp_X]/4.5 mL
INACTIVE INGREDIENTS: ALCOHOL; GLYCERIN; POTASSIUM SORBATE; WATER

SnoreStop Throat Spray 120

Ingredients (HPUS):

Belladonna 6x, Ephedra vulg. 6x, Histaminium hydrochloricum 12x, Hydrastis 6x, Kali bic 6x, Nux vom. 4x, 6x, Teucrium mar. 6x.

Inactive Ingredients:

Alcohol (100 micro centiliters per spray), Glycerin, Potassium sorbate, Purified water (75%).

Uses:

Temporarily relieves symptoms of non-apneic snoring. Individual results may vary.

Warnings:

Warnings: Use only as directed. Keep this out of reach of children. If pregnant or breastfeeding, ask a doctor before use. Stop use and ask a doctor if symptoms do not improve in 7 days.

Use only if tamper resistant seal around the bottle is unbroken.

Store below 77°F (25°C)

Keep out of reach of children.

Keep this out of reach of children

Directions:

Adults: Shake bottle before each use. Lift yellow arm up to a right angle.
On first use, prime pump by depressing several times. Spray once under the tongue and once in the back of the throat at bedtime. Do not take with water. Use 30 mins apart from any food, water, or medicine. Please allow3-5 days for initial treatment.

For Maximum Results, use in conjunction with SnoreStop Nasal Spray. May be used up to 4 times a day.

DOES NOT TREAT SLEEP APNEA

Purpose:

Temporarily helps stop or reduce symptoms of non-apneic snoring. Individual results may vary.

Other information

Use only if tamper resistant seal around the bottle is unbroken.

Store below 77°F (25°C)

Distributed by Green Pharmaceuticals, Camarillo, CA 93012, USA.
Questions? Call 1-877-SNORESTOP or visit www.snorestop.com

Questions?

Questions? Call 1-877-SNORESTOP or visit www.snorestop.com